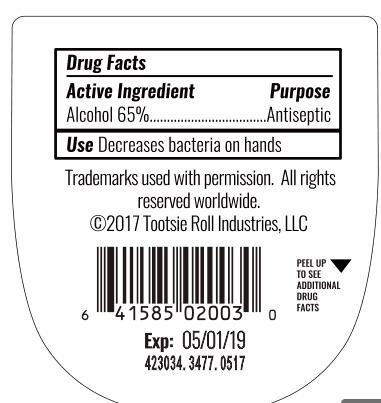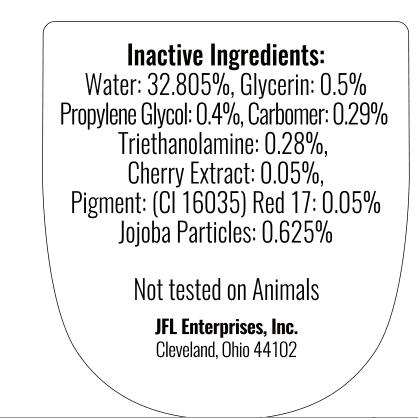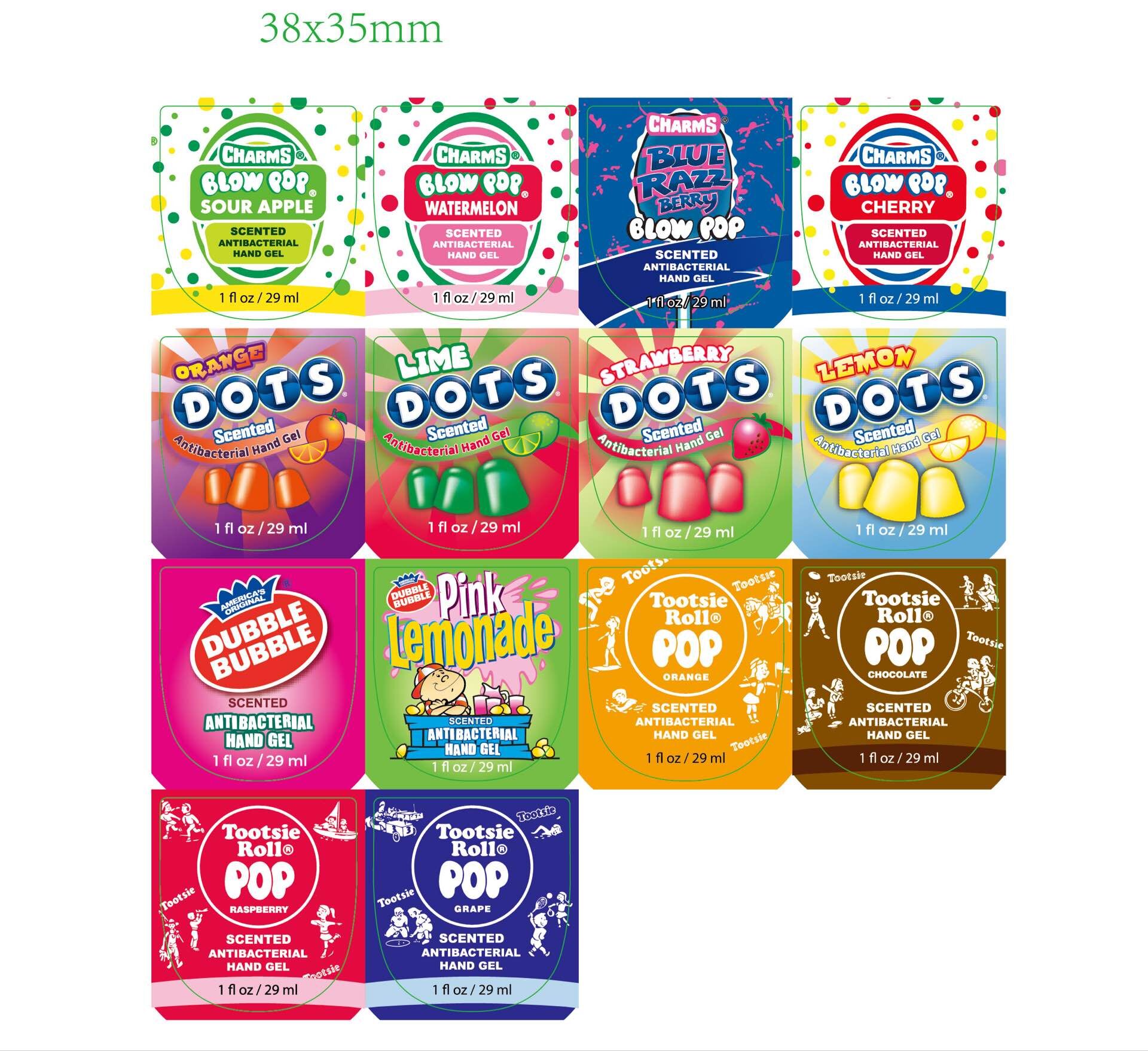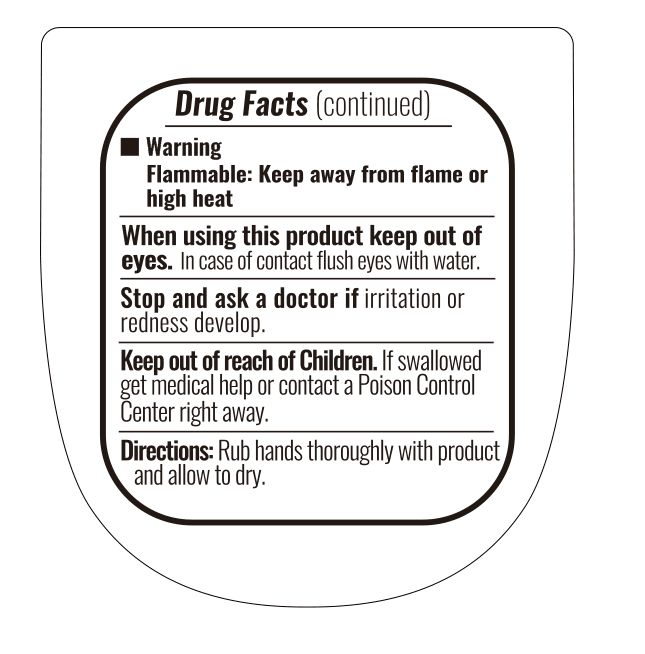 DRUG LABEL: Hand sanitizer
NDC: 70939-002 | Form: SWAB
Manufacturer: Dongguang Shuoguo Silicone Products Co., Ltd.
Category: otc | Type: HUMAN OTC DRUG LABEL
Date: 20200201

ACTIVE INGREDIENTS: ALCOHOL 65 mL/100 mL
INACTIVE INGREDIENTS: PROPYLENE GLYCOL; WATER; TRIETHANOLAMINE BENZOATE; GLYCERIN; CARBOMER 934; JOJOBA OIL; CHERRY

ASSURED ANTIBACTERIAL WET WIPES

Active ingredient

Alcohol 65%

Purpose

Antiseptic

Use

to decrease bacteria on the hands

Warnings

flammable:keep away from flame or high heat.

when useing this product keep out of eyes.in case of contact flush eyes with water.

stop and ask a doctor if irritation or redness develop

Keep out of reach of children

if swallowed
get medical help or contact a Poison Control Center right away.

Directions

Rub hands thoroughly with product and allow to dry

INACTIVE INGREDIENT

Water ,Glycerin, Propylene Glycol, Carbomer, Triethanolamine